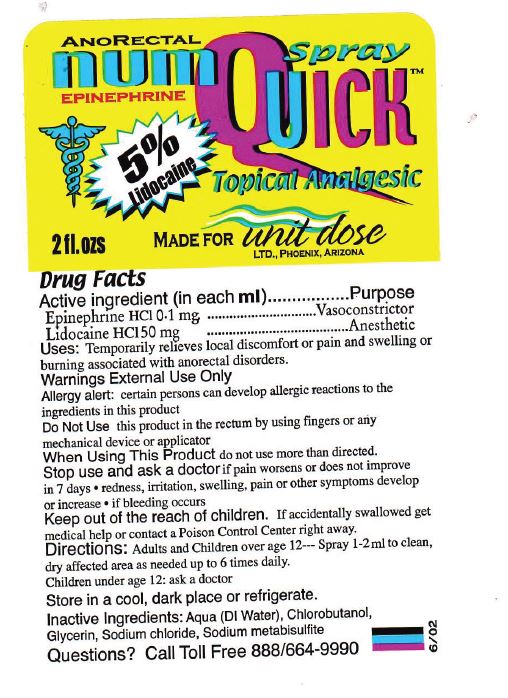 DRUG LABEL: Numquick Analgesic
NDC: 67194-008 | Form: SPRAY
Manufacturer: Unit Dose, Ltd.
Category: otc | Type: HUMAN OTC DRUG LABEL
Date: 20240228

ACTIVE INGREDIENTS: EPINEPHRINE HYDROCHLORIDE 0.1 mg/1 mL; LIDOCAINE HYDROCHLORIDE 50 mg/1 mL
INACTIVE INGREDIENTS: WATER; CHLOROBUTANOL; GLYCERIN; EDETATE SODIUM; SODIUM METABISULFITE

Numquick Analgesic

Active ingredient

Epinephrine HCl 0.1 mg

Lidocaine HCl 50 mg

Purpose

Vasoconstrictor

Anesthetic

Uses:

Temporarily relieves local discomfort or pain and swelling or burning associated with anorectal disorders.

Warnings

External use only

certain persons can develop allergic reactions to the ingredients in this product Allergy alert:

Allergy alert:

certain persons can develop allergic reactions to the ingredients in this product

Do Not Use

this product in the rectum by using fingers or any mechanical device or applicator

When Using This Product

do not use more than directed.

Stop use and ask a doctor

if pain worsens or does not improve in 7 days

- redness, irritation, swelling, pain or other symptoms develop or increase
- if bleeding occurs

Keep out of the reach of children.

If accidentally swallowed get medical help or contact a Poison Control Center right away.

Directions:

Adults and Children over age 12 Spray 1-2ml to clean, dry affected area as needed up to 6 times daily. ---

Children under age 12: ask a doctor

Store in a cool, dark place or refrigerate.

Inactive Ingredients:

Aqua (DI Water), Chlorobutanol, Glycerin, Sodium chloride, Sodium metabisulfite

Questions?

Call Toll Free 888/664-9990